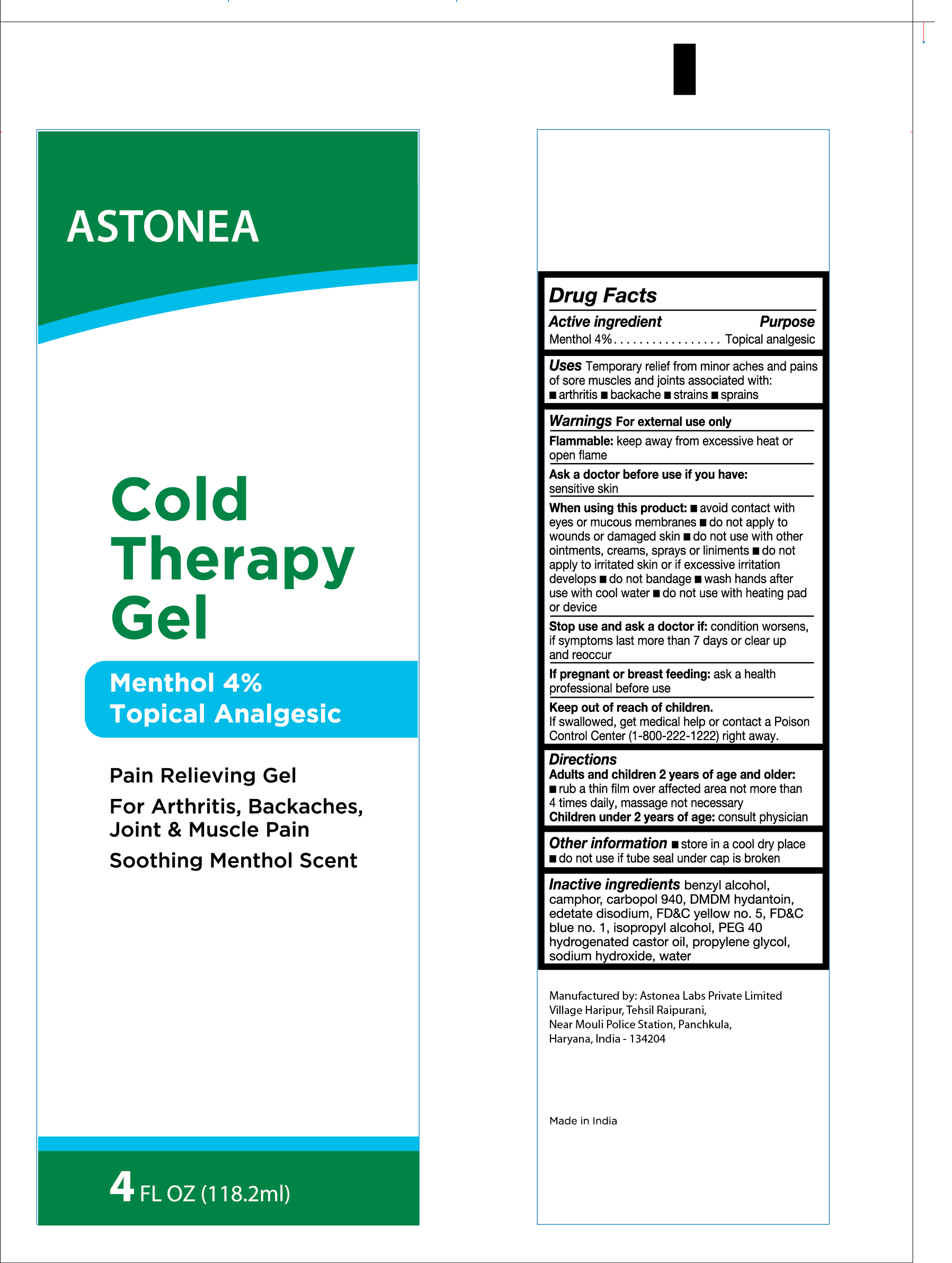 DRUG LABEL: ASTONEA COLD THERAPY
NDC: 77338-007 | Form: GEL
Manufacturer: ASTONEA LABS PRIVATE LIMITED
Category: otc | Type: HUMAN OTC DRUG LABEL
Date: 20240312

ACTIVE INGREDIENTS: MENTHOL 4 g/100 g
INACTIVE INGREDIENTS: POLYETHYLENE GLYCOL 2000; GLYCERIN; DMDM HYDANTOIN; EDETATE SODIUM; CARBOMER 940; ISOPROPYL ALCOHOL; FD&C YELLOW NO. 5; FD&C BLUE NO. 1; HYDROGENATED CASTOR OIL; SODIUM HYDROXIDE; WATER; CAMPHOR (SYNTHETIC)

ASTONEA COLD THERAPY 4% MENTHOL

ACTIVE INGREDIENT

Menthol 4%

PURPOSE

Topical Analgesic

INDICATIONS AND USAGE

Temporary relief from minor aches and pains of sore muscles and joints associated with:

arthritis

backache

strains

sprains

WARNINGS

For external use only

Flammable:Keep away from excessive heat or open flame

Ask a doctor before use if you have: sensitive skin

Stop use and ask a doctor if

condition worsens or symptoms persist for more than 7 days or clear up and occur again within a few days.

When using this product

■avoid contact with eyes or mucous membranes ■do not apply to wounds or damaged skin ■ do not use with other ointments, creams, sprays or liniments ■ do not apply to irritated skin or if excessive irritation develops ■do not bandage ■ wash hands alter use with cool water ■do not use with heating pad or device

PREGNANCY OR BREAST FEEDING

If pregnant or breastfeeding, ask a health professional before use

Keep out of reach of children: If accidentally ingested, get medical help or contact a poison Control immediately (1800-222-1222)

Directions

Adults and children 2 years of age and older:Rub a thin film over affected areas not more than daily: massage not necessary

Children under 2 years of age :Consult physician

INACTIVE INGREDIENT

camphor, carbopol 940, DMDM hydantoin, edetate disodium, FD&C yellow no. 5, FD&C blue no. 1, isopropyl alcohol, PEG 40

hydrogenated castor oil, propylene glycol, sodium hydroxide, water